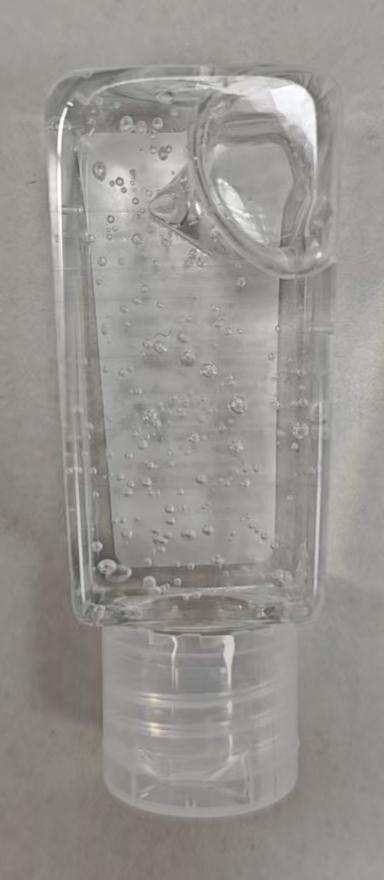 DRUG LABEL: palm party
NDC: 87322-1614 | Form: GEL
Manufacturer: Dongyang Loulee Cosmetics Co.,Ltd.
Category: otc | Type: HUMAN OTC DRUG LABEL
Date: 20260116

ACTIVE INGREDIENTS: ALCOHOL 60 mL/100 mL
INACTIVE INGREDIENTS: FRAGRANCE 13576 5 mL/100 mL; PHENOXYETHANOL 0.4 mL/100 mL; WATER 34.2 mL/100 mL; ACRYLATES/C10-30 ALKYL ACRYLATE CROSSPOLYMER (60000 MPA.S) 0.2 mL/100 mL; ARGININE 0.2 mL/100 mL

Active ingredient(s)

Alcohol 60%

Purpose(s)

Antisepti

Uses

Hand sanitizer to help reduce bacteria that potentially can cause disease. For use when soap and water are not available.

Warnings

- Flammable. Keep away from fire or flame.
- For external use only.

Do not use

In the eyes. In case of contact, rinse eyes thoroughly with water.

Stop use and ask a doctor if

Irritation or rash appears and lasts.

Keep out of reach of children

If swallowed, get medical help or contact a Poison Control Center right away.

Directions

- Place enough product on hands to cover all surfaces. Rub hands together until dry.
- Supervise children under 6 years of age when using this product to avoid swallowing.

Inactive ingredients

WATER, FRAGRANCE, ACRYLATES/C10-30 ALKYL ACRYLATE CROSSPOLYMER, ARGININE, PHENOXYETHANOL

Questions or comments?

213-396-1046 / MalachiPerez291@gmail.com